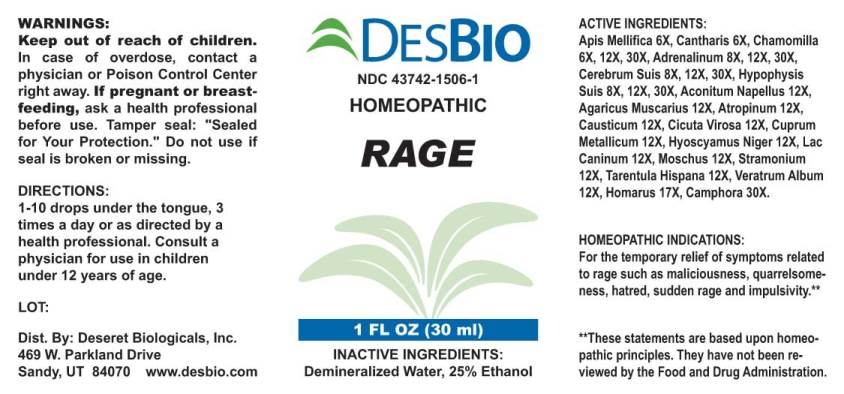 DRUG LABEL: Rage
NDC: 43742-1506 | Form: LIQUID
Manufacturer: Deseret Biologicals, Inc.
Category: homeopathic | Type: HUMAN OTC DRUG LABEL
Date: 20240911

ACTIVE INGREDIENTS: APIS MELLIFERA 6 [hp_X]/1 mL; LYTTA VESICATORIA 6 [hp_X]/1 mL; MATRICARIA CHAMOMILLA WHOLE 6 [hp_X]/1 mL; EPINEPHRINE 8 [hp_X]/1 mL; SUS SCROFA CEREBRUM 8 [hp_X]/1 mL; SUS SCROFA PITUITARY GLAND 8 [hp_X]/1 mL; ACONITUM NAPELLUS WHOLE 12 [hp_X]/1 mL; AMANITA MUSCARIA FRUITING BODY 12 [hp_X]/1 mL; ATROPINE 12 [hp_X]/1 mL; CAUSTICUM 12 [hp_X]/1 mL; CICUTA VIROSA ROOT 12 [hp_X]/1 mL; COPPER 12 [hp_X]/1 mL; HYOSCYAMUS NIGER 12 [hp_X]/1 mL; CANIS LUPUS FAMILIARIS MILK 12 [hp_X]/1 mL; MOSCHUS MOSCHIFERUS MUSK SAC RESIN 12 [hp_X]/1 mL; DATURA STRAMONIUM 12 [hp_X]/1 mL; LYCOSA TARANTULA 12 [hp_X]/1 mL; VERATRUM ALBUM ROOT 12 [hp_X]/1 mL; HOMARUS AMERICANUS DIGESTIVE FLUID 17 [hp_X]/1 mL; CAMPHOR (NATURAL) 30 [hp_X]/1 mL
INACTIVE INGREDIENTS: WATER; ALCOHOL

Drug Facts:

ACTIVE INGREDIENTS:

Apis Mellifica 6X, Cantharis 6X, Chamomilla 6X, 12X, 30X, Adrenalinum 8X, 12X, 30X, Cerebrum Suis 8X, 12X, 30X, Hypophysis Suis 8X, 12X, 30X, Aconitum Napellus 12X, Agaricus Muscarius 12X, Atropinum 12X, Causticum 12X, Cicuta Virosa 12X, Cuprum Metallicum 12X, Hyoscyamus Niger 12X, Lac Caninum V, Moschus 12X, Stramonium 12X, Tarentula Hispana 12X, Veratrum Album 12X, Homarus 17X, Camphora 30X.

HOMEOPATHIC INDICATIONS:

May temporarily relieve symptoms related to rage such as maliciousness, quarrelsomeness, hatred, sudden rage and impulsivity.

**These statements are based upon traditional homeopathic principles. They have not been reviewed by the Food and Drug Administration.

WARNINGS:

Keep out of reach of children. In case of overdose, contact physician or a Poison Control Center right away.

If pregnant or breast-feeding, ask a health professional before use.

Tamper seal: "Sealed for Your Protection." Do not use if seal is broken or missing.

Keep out of reach of children. In case of overdose, contact physician or a Poison Control Center right away.

DIRECTIONS:

1-10 drops under the tongue, 3 times a day or as directed by a health professional. Consult a physician for use in children under 12 years of age.

HOMEOPATHIC INDICATIONS:

May temporarily relieve symptoms related to rage such as maliciousness, quarrelsomeness, hatred, sudden rage and impulsivity.

**These statements are based upon traditional homeopathic principles. They have not been reviewed by the Food and Drug Administration.

INACTIVE INGREDIENTS:

Demineralized Water, 25% Ethanol

QUESTIONS:

Dist. By: Deseret Biologicals, Inc.

469 W. Parkland Drive

Sandy, UT 84070 www.desbio.com

PACKAGE LABEL DISPLAY:

DESBIO

NDC 43742-1506-1

HOMEOPATHIC

RAGE

1 FL OZ (30 ml)